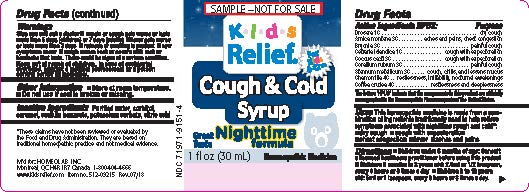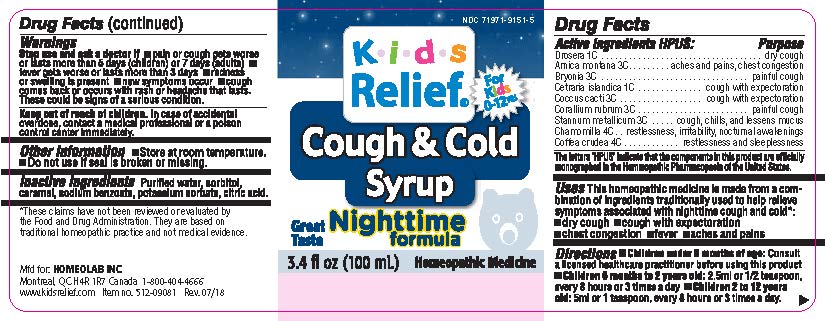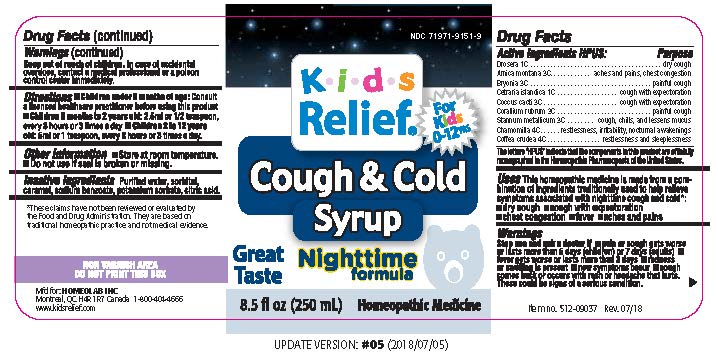 DRUG LABEL: Kids Relief
NDC: 63388-915 | Form: LIQUID
Manufacturer: Laboratoire Atlas Inc
Category: homeopathic | Type: HUMAN OTC DRUG LABEL
Date: 20251008

ACTIVE INGREDIENTS: DROSERA ROTUNDIFOLIA FLOWERING TOP 1 [hp_C]/100 mL; ARNICA MONTANA 3 [hp_C]/100 mL; BRYONIA ALBA WHOLE 3 [hp_C]/100 mL; CETRARIA ISLANDICA SUBSP. ISLANDICA 1 [hp_C]/100 mL; PROTORTONIA CACTI 3 [hp_C]/100 mL; TIN 3 [hp_C]/100 mL; CHAMOMILE 4 [hp_C]/100 mL; ARABICA COFFEE BEAN 4 [hp_C]/100 mL; CORALLIUM RUBRUM WHOLE 3 [hp_C]/100 mL
INACTIVE INGREDIENTS: WATER; SORBITOL; CARAMEL; SODIUM BENZOATE; POTASSIUM SORBATE; CITRIC ACID MONOHYDRATE

Active Ingredients HPUS

Drosera 1C

Arnica Montana 3C

Bryonia 3C

Cetraria islandica 3C

Coccus cacti 3C

Corallium rubrum 3C

Stannum metallicum 3C

Chamomilla 4C

Coffee crudea 4C

Purpose

Drosera 1C...........................dry cough

Arnica Montana 3C.................aches and pains, chest congestion

Bryonia 3C............................painful cough

Cetraria islandica 3C...............cough with expectoration

Coccus cacti 3C......................cough with expectoration

Corallium rubrum 3C...............painful cough

Stannum metallicum 3C...........cough, chills and lessens mucus

Chamomilla 4C.......................restlessness, irritability, nocturnal awakenings

Coffee crudea 4C....................restlessness and sleeplessness

The letters "HPUS" indicate that the components in this product are officially

monographed in the Homeopathic Pharmacopoeia of the United States

INDICATIONS AND USAGE

UsesThis homeopathic medicine is made from a combination

of ingredients traditionally used to help relieve

symptoms associated with nighttime cough and cold:

•dry cough •cough with expectoration

•chest congestion •fever •aches and pains

Warnings

Stop use and ask a doctor if •pain or cough gets worse or lasts

more than 5 days (children) or 7 days (adults) •fever gets worse

or lasts more than 3 days •redness or swelling is present •new

symptoms occur •cough comes back or occurs with rash or

headache that lasts. These could be signs of a serious condition.

Keep out of reach of children.In case of accidental

overdose, contact a medical professional or a poison

control center immediately.

DOSAGE AND ADMINISTRATION

Directions • Chidren under 6 months of age: Consult

a licensed healthcare professional before using this product

• Children 6 months to 2 years old: 2.5ml or 1/2 teaspoon,

every 8 hours or 3 times a day • Children 2 to 12 years

old: 5ml or 1 teaspoon, every 8 hours or 3 times a day.

Other information•Store at room temperature.

•Do not use if seal is broken or missing.

Inactive ingredientsPurified water, sorbitol,

caramel, sodium benzoate, potassium sorbate, citric acid